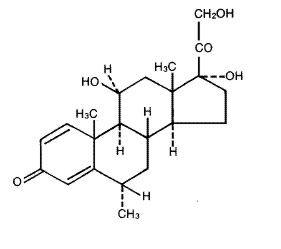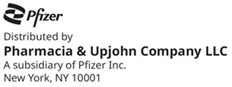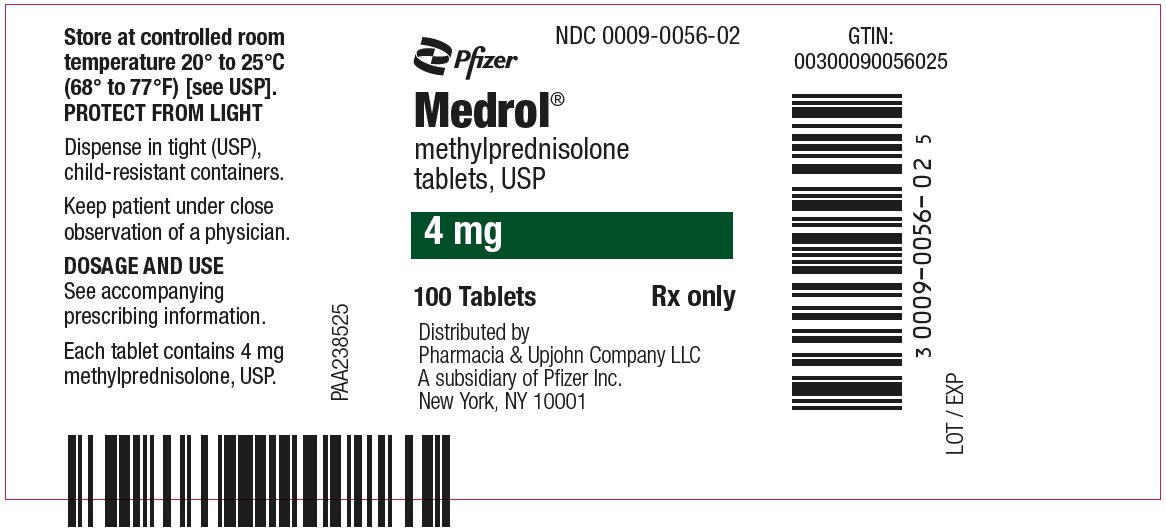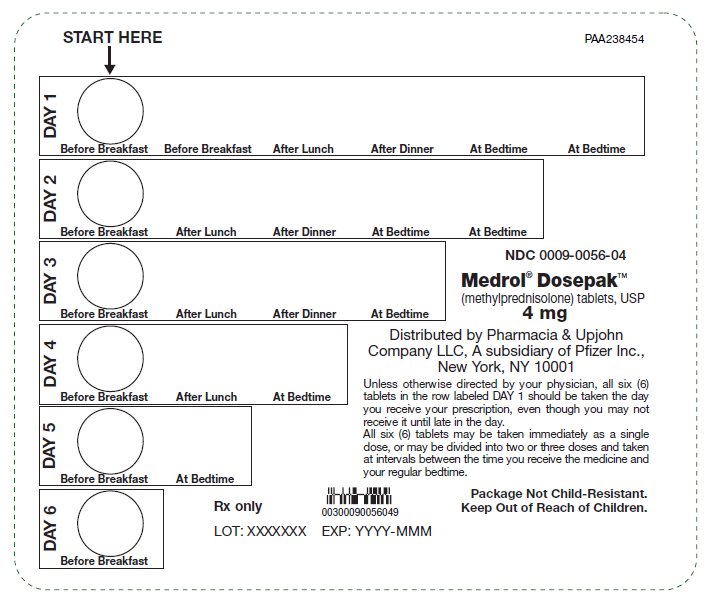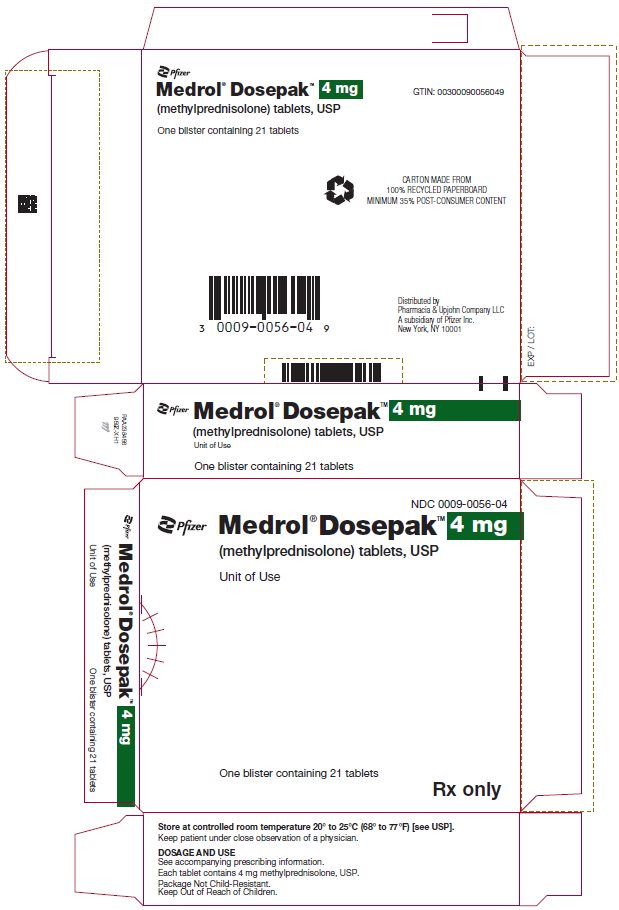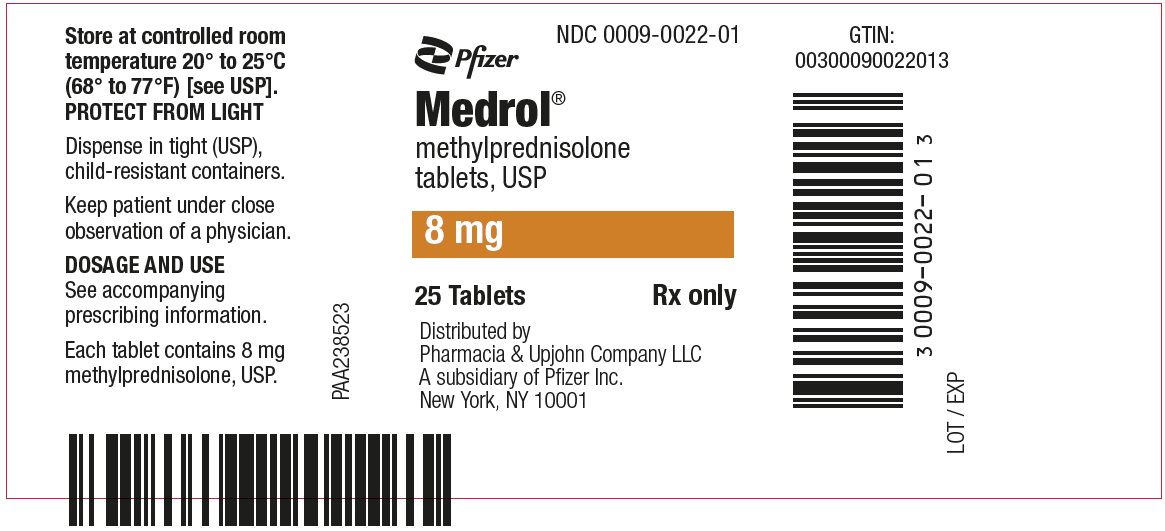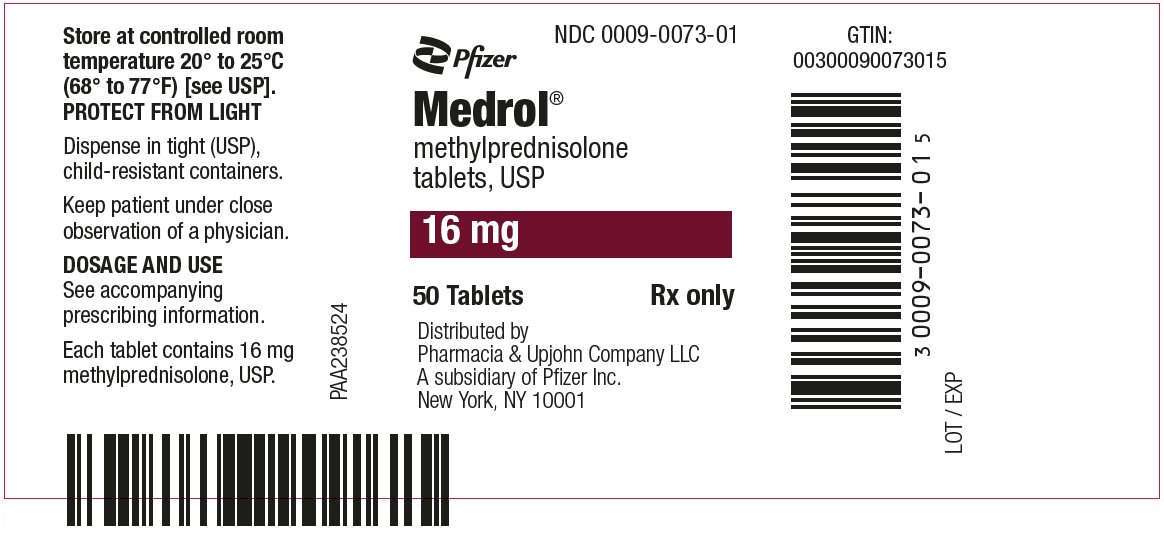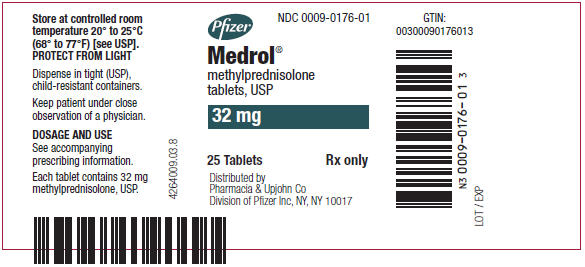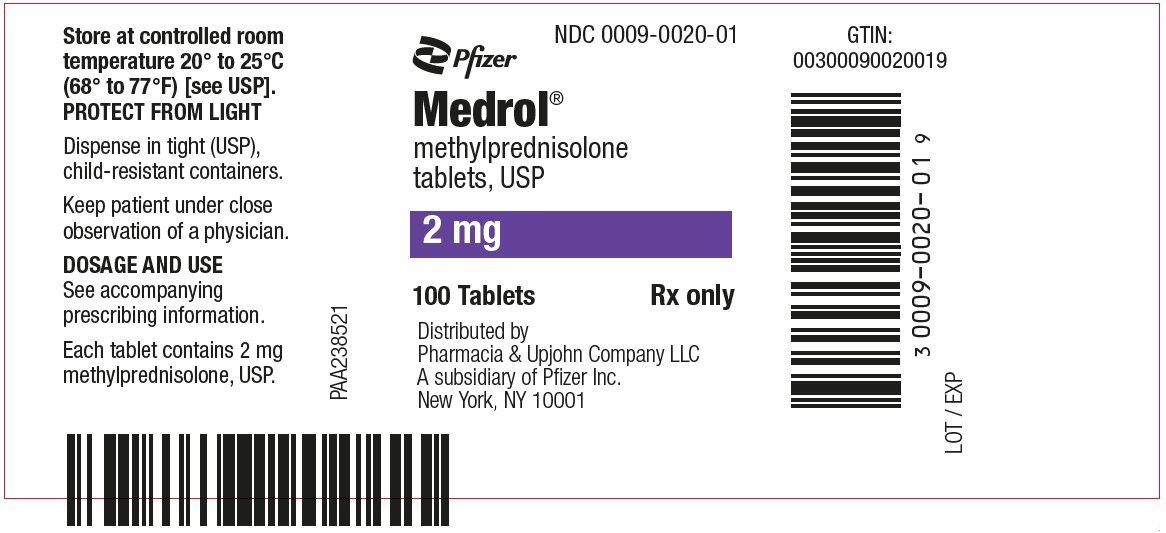 DRUG LABEL: Medrol
NDC: 0009-0049 | Form: TABLET
Manufacturer: Pharmacia & Upjohn Company LLC
Category: prescription | Type: HUMAN PRESCRIPTION DRUG LABEL
Date: 20251114

ACTIVE INGREDIENTS: METHYLPREDNISOLONE 2 mg/1 1
INACTIVE INGREDIENTS: CALCIUM STEARATE; STARCH, CORN; LACTOSE, UNSPECIFIED FORM; MINERAL OIL; SORBIC ACID; SUCROSE

Medrol®
methylprednisolone
tablets, USP

DESCRIPTION

MEDROL Tablets contain methylprednisolone which is a glucocorticoid. Glucocorticoids are adrenocortical steroids, both naturally occurring and synthetic, which are readily absorbed from the gastrointestinal tract. Methylprednisolone occurs as a white to practically white, odorless, crystalline powder. It is sparingly soluble in alcohol, in dioxane, and in methanol, slightly soluble in acetone, and in chloroform, and very slightly soluble in ether. It is practically insoluble in water.

The chemical name for methylprednisolone is pregna-1,4-diene-3,20-dione, 11,17,21-trihydroxy-6-methyl-, (6α,11β)-and the molecular weight is 374.48. The structural formula is represented below:

Each MEDROL Tablet for oral administration contains 2 mg, 4 mg, 8 mg, 16 mg or 32 mg of methylprednisolone.

Inactive ingredients:

2 mg | 4 mg and 8 mg
Calcium Stearate | Calcium Stearate
Corn Starch | Corn Starch
Lactose | Lactose
Mineral Oil | Sucrose
Sorbic Acid
Sucrose
16 mg and 32 mg
Calcium Stearate
Corn Starch
Lactose
Mineral Oil
Sucrose

ACTIONS

Naturally occurring glucocorticoids (hydrocortisone and cortisone), which also have salt-retaining properties, are used as replacement therapy in adrenocortical deficiency states. Their synthetic analogs are primarily used for their potent anti-inflammatory effects in disorders of many organ systems.

Glucocorticoids cause profound and varied metabolic effects. In addition, they modify the body's immune responses to diverse stimuli.

INDICATIONS AND USAGE

MEDROL Tablets are indicated in the following conditions:

1. Endocrine Disorders

Primary or secondary adrenocortical insufficiency (hydrocortisone or cortisone is the first choice; synthetic analogs may be used in conjunction with mineralocorticoids where applicable; in infancy mineralocorticoid supplementation is of particular importance).

Congenital adrenal hyperplasia

Nonsuppurative thyroiditis

Hypercalcemia associated with cancer

2. Rheumatic Disorders

As adjunctive therapy for short-term administration (to tide the patient over an acute episode or exacerbation) in:

Rheumatoid arthritis, including juvenile rheumatoid arthritis (selected cases may require low-dose maintenance therapy)

Ankylosing spondylitis

Acute and subacute bursitis

Synovitis of osteoarthritis

Acute nonspecific tenosynovitis

Post-traumatic osteoarthritis

Psoriatic arthritis

Epicondylitis

Acute gouty arthritis

3. Collagen Diseases

During an exacerbation or as maintenance therapy in selected cases of:

Systemic lupus erythematosus

Systemic dermatomyositis (polymyositis)

Acute rheumatic carditis

4. Dermatologic Diseases

Bullous dermatitis herpetiformis

Severe erythema multiforme

(Stevens-Johnson syndrome)

Severe seborrheic dermatitis

Exfoliative dermatitis

Mycosis fungoides

Pemphigus

Severe psoriasis

5. Allergic States

Control of severe or incapacitating allergic conditions intractable to adequate trials of conventional treatment:

Seasonal or perennial allergic rhinitis

Drug hypersensitivity reactions

Serum sickness

Contact dermatitis

Bronchial asthma

Atopic dermatitis

6. Ophthalmic Diseases

Severe acute and chronic allergic and inflammatory processes involving the eye and its adnexa such as:

Allergic corneal marginal ulcers

Herpes zoster ophthalmicus

Anterior segment inflammation

Diffuse posterior uveitis and choroiditis

Sympathetic ophthalmia

Keratitis

Optic neuritis

Allergic conjunctivitis

Chorioretinitis

Iritis and iridocyclitis

7. Respiratory Diseases

Symptomatic sarcoidosis

Berylliosis

Loeffler's syndrome not manageable by other means

Fulminating or disseminated pulmonary tuberculosis when used concurrently with appropriate antituberculous chemotherapy

Aspiration pneumonitis

8. Hematologic Disorders

Idiopathic thrombocytopenic purpura in adults

Secondary thrombocytopenia in adults

Acquired (autoimmune) hemolytic anemia

Erythroblastopenia (RBC anemia)

Congenital (erythroid) hypoplastic anemia

9. Neoplastic Diseases

For palliative management of:

Leukemias and lymphomas in adults

Acute leukemia of childhood

10. Edematous States

To induce a diuresis or remission of proteinuria in the nephrotic syndrome, without uremia, of the idiopathic type or that due to lupus erythematosus.

11. Gastrointestinal Diseases

To tide the patient over a critical period of the disease in:

Ulcerative colitis

Regional enteritis

12. Nervous System

Acute exacerbations of multiple sclerosis

13. Miscellaneous

Tuberculous meningitis with subarachnoid block or impending block when used concurrently with appropriate antituberculous chemotherapy.

Trichinosis with neurologic or myocardial involvement.

CONTRAINDICATIONS

Systemic fungal infections and known hypersensitivity to components.

WARNINGS

In patients on corticosteroid therapy subjected to unusual stress, increased dosage of rapidly acting corticosteroids before, during, and after the stressful situation is indicated.

Immunosuppression and Increased Risk of Infection

Corticosteroids, including MEDROL, suppress the immune system and increase the risk of infection with any pathogen, including viral, bacterial, fungal, protozoan, or helminthic pathogens. Corticosteroids can:

- Reduce resistance to new infections
- Exacerbate existing infections
- Increase the risk of disseminated infections
- Increase the risk of reactivation or exacerbation of latent infections
- Mask some signs of infection

Corticosteroid-associated infections can be mild but can be severe and at times fatal. The rate of infectious complications increases with increasing corticosteroid dosages.

Monitor for the development of infection and consider MEDROL withdrawal or dosage reduction as needed.

Tuberculosis

If MEDROL is used to treat a condition in patients with latent tuberculosis or tuberculin reactivity, reactivation of tuberculosis may occur. Closely monitor such patients for reactivation. During prolonged MEDROL therapy, patients with latent tuberculosis or tuberculin reactivity should receive chemoprophylaxis.

Varicella Zoster and Measles Viral Infections

Varicella and measles can have a serious or even fatal course in non-immune patients taking corticosteroids, including MEDROL. In corticosteroid-treated patients who have not had these diseases or are non-immune, particular care should be taken to avoid exposure to varicella and measles:

- If a MEDROL-treated patient is exposed to varicella, prophylaxis with varicella zoster immune globulin may be indicated. If varicella develops, treatment with antiviral agents may be considered.
- If a MEDROL-treated patient is exposed to measles, prophylaxis with immunoglobulin may be indicated.

Hepatitis B Virus Reactivation

Hepatitis B virus reactivation can occur in patients who are hepatitis B carriers treated with immunosuppressive dosages of corticosteroids, including MEDROL. Reactivation can also occur infrequently in corticosteroid-treated patients who appear to have resolved hepatitis B infection.

Screen patients for hepatitis B infection before initiating immunosuppressive (e.g., prolonged) treatment with MEDROL. For patients who show evidence of hepatitis B infection, recommend consultation with physicians with expertise in managing hepatitis B regarding monitoring and consideration for hepatitis B antiviral therapy.

Fungal Infections

Corticosteroids, including MEDROL, may exacerbate systemic fungal infections; therefore, avoid MEDROL use in the presence of such infections unless MEDROL is needed to control drug reactions. For patients on chronic MEDROL therapy who develop systemic fungal infections, MEDROL withdrawal or dosage reduction is recommended.

Amebiasis

Corticosteroids, including MEDROL, may activate latent amebiasis. Therefore, it is recommended that latent amebiasis or active amebiasis be ruled out before initiating MEDROL in patients who have spent time in the tropics or patients with unexplained diarrhea.

Strongyloides Infestation

Corticosteroids, including MEDROL, should be used with great care in patients with known or suspected Strongyloides (threadworm) infestation. In such patients, corticosteroid-induced immunosuppression may lead to Strongyloides hyperinfection and dissemination with widespread larval migration, often accompanied by severe enterocolitis and potentially fatal gram-negative septicemia.

Cerebral Malaria

Avoid corticosteroids, including MEDROL, in patients with cerebral malaria.

Ophthalmic Effects

Prolonged use of corticosteroids may produce posterior subcapsular cataracts, glaucoma with possible damage to the optic nerves, and may enhance the establishment of secondary ocular infections due to fungi or viruses.

Kaposi’s Sarcoma

Kaposi’s sarcoma has been reported to occur in patients receiving corticosteroid therapy, most often for chronic conditions. Discontinuation of corticosteroids may result in clinical improvement of Kaposi’s sarcoma.

Hypertension, Volume Overload, and Hypokalemia

Average and large doses of hydrocortisone or cortisone can cause elevation of blood pressure, salt and water retention, and increased excretion of potassium. These effects are less likely to occur with the synthetic derivatives except when used in large doses. Dietary salt restriction and potassium supplementation may be necessary. All corticosteroids increase calcium excretion.

Vaccination

Administration of live or live, attenuated vaccines is contraindicated in patients receiving immunosuppressive doses of corticosteroids. Killed or inactivated vaccines may be administered to patients receiving immunosuppressive doses of corticosteroids; however, the response to such vaccines may be diminished. Indicated immunization procedures may be undertaken in patients receiving nonimmunosuppressive doses of corticosteroids.

Usage in Pregnancy

Since adequate human reproduction studies have not been done with corticosteroids, the use of these drugs in pregnancy, nursing mothers or women of child-bearing potential requires that the possible benefits of the drug be weighed against the potential hazards to the mother and embryo or fetus. Infants born of mothers who have received substantial doses of corticosteroids during pregnancy, should be carefully observed for signs of hypoadrenalism.

PRECAUTIONS

General Precautions

Drug-induced secondary adrenocortical insufficiency may be minimized by gradual reduction of dosage. This type of relative insufficiency may persist for months after discontinuation of therapy; therefore, in any situation of stress occurring during that period, hormone therapy should be reinstituted. Since mineralocorticoid secretion may be impaired, salt and/or a mineralocorticoid should be administered concurrently.

There is an enhanced effect of corticosteroids on patients with hypothyroidism and in those with cirrhosis.

Corticosteroids should be used cautiously in patients with ocular herpes simplex because of possible corneal perforation.

The lowest possible dose of corticosteroid should be used to control the condition under treatment, and when reduction in dosage is possible, the reduction should be gradual.

Psychic derangements may appear when corticosteroids are used, ranging from euphoria, insomnia, mood swings, personality changes, and severe depression, to frank psychotic manifestations. Also, existing emotional instability or psychotic tendencies may be aggravated by corticosteroids.

Caution is required in patients with systemic sclerosis because an increased incidence of scleroderma renal crisis has been observed with corticosteroids, including methylprednisolone.

Steroids should be used with caution in nonspecific ulcerative colitis, if there is a probability of impending perforation, abscess or other pyogenic infection; diverticulitis; fresh intestinal anastomoses; active or latent peptic ulcer; renal insufficiency; hypertension; osteoporosis; and myasthenia gravis.

Growth and development of infants and children on prolonged corticosteroid therapy should be carefully observed.

Although controlled clinical trials have shown corticosteroids to be effective in speeding the resolution of acute exacerbations of multiple sclerosis, they do not show that corticosteroids affect the ultimate outcome or natural history of the disease. The studies do show that relatively high doses of corticosteroids are necessary to demonstrate a significant effect. (See DOSAGE AND ADMINISTRATION.)

Since complications of treatment with glucocorticoids are dependent on the size of the dose and the duration of treatment, a risk/benefit decision must be made in each individual case as to dose and duration of treatment and as to whether daily or intermittent therapy should be used.

In post marketing experience, tumor lysis syndrome (TLS) has been reported in patients with malignancies, including hematological malignancies and solid tumors, following the use of systemic corticosteroids alone or in combination with other chemotherapeutic agents. Patients at high risk of TLS, such as patients with tumors that have a high proliferative rate, high tumor burden and high sensitivity to cytotoxic agents, should be monitored closely and appropriate precautions should be taken.

DRUG INTERACTIONS

The pharmacokinetic interactions listed below are potentially clinically important. Mutual inhibition of metabolism occurs with concurrent use of cyclosporin and methylprednisolone; therefore, it is possible that adverse events associated with the individual use of either drug may be more apt to occur. Convulsions have been reported with concurrent use of methylprednisolone and cyclosporin. Drugs that induce hepatic enzymes such as phenobarbital, phenytoin and rifampin may increase the clearance of methylprednisolone and may require increases in methylprednisolone dose to achieve the desired response. Drugs such as troleandomycin and ketoconazole may inhibit the metabolism of methylprednisolone and thus decrease its clearance. Therefore, the dose of methylprednisolone should be titrated to avoid steroid toxicity.

Methylprednisolone may increase the clearance of chronic high dose aspirin. This could lead to decreased salicylate serum levels or increase the risk of salicylate toxicity when methylprednisolone is withdrawn. Aspirin should be used cautiously in conjunction with corticosteroids in patients suffering from hypoprothrombinemia.

The effect of methylprednisolone on oral anticoagulants is variable. There are reports of enhanced as well as diminished effects of anticoagulant when given concurrently with corticosteroids. Therefore, coagulation indices should be monitored to maintain the desired anticoagulant effect.

Information for the Patient

Persons who are on immunosuppressant doses of corticosteroids should be warned to avoid exposure to chickenpox or measles. Patients should also be advised that if they are exposed, medical advice should be sought without delay.

ADVERSE REACTIONS

Fluid and Electrolyte Disturbances

- Sodium retention
- Congestive heart failure in susceptible patients
- Hypertension
- Fluid retention
- Potassium loss
- Hypokalemic alkalosis

Musculoskeletal

- Muscle weakness
- Loss of muscle mass
- Steroid myopathy
- Osteoporosis
- Tendon rupture, particularly of the Achilles tendon
- Vertebral compression fractures
- Aseptic necrosis of femoral and humeral heads
- Pathologic fracture of long bones

Gastrointestinal

- Peptic ulcer with possible perforation and hemorrhage
- Pancreatitis
- Abdominal distention
- Ulcerative esophagitis

Increases in alanine transaminase (ALT, SGPT), aspartate transaminase (AST, SGOT), and alkaline phosphatase have been observed following corticosteroid treatment. These changes are usually small, not associated with any clinical syndrome and are reversible upon discontinuation.

Dermatologic

- Impaired wound healing
- Petechiae and ecchymoses
- May suppress reactions to skin tests
- Thin fragile skin
- Facial erythema
- Increased sweating

Neurological

- Increased intracranial pressure with papilledema (pseudo-tumor cerebri) usually after treatment
- Convulsions
- Vertigo
- Headache

Endocrine

- Development of Cushingoid state
- Suppression of growth in children
- Secondary adrenocortical and pituitary unresponsiveness, particularly in times of stress, as in trauma, surgery or illness
- Menstrual irregularities
- Decreased carbohydrate tolerance
- Manifestations of latent diabetes mellitus
- Increased requirements of insulin or oral hypoglycemic agents in diabetics

Ophthalmic

- Posterior subcapsular cataracts
- Increased intraocular pressure
- Glaucoma
- Exophthalmos

Metabolic

- Negative nitrogen balance due to protein catabolism

Vascular

- Flushing

The following additional reactions have been reported following oral as well as parenteral therapy: Urticaria and other allergic, anaphylactic or hypersensitivity reactions.

DOSAGE AND ADMINISTRATION

The initial dosage of MEDROL Tablets may vary from 4 mg to 48 mg of methylprednisolone per day depending on the specific disease entity being treated. In situations of less severity lower doses will generally suffice while in selected patients higher initial doses may be required. The initial dosage should be maintained or adjusted until a satisfactory response is noted. If after a reasonable period of time there is a lack of satisfactory clinical response, MEDROL should be discontinued and the patient transferred to other appropriate therapy.

IT SHOULD BE EMPHASIZED THAT DOSAGE REQUIREMENTS ARE VARIABLE AND MUST BE INDIVIDUALIZED ON THE BASIS OF THE DISEASE UNDER TREATMENT AND THE RESPONSE OF THE PATIENT. After a favorable response is noted, the proper maintenance dosage should be determined by decreasing the initial drug dosage in small decrements at appropriate time intervals until the lowest dosage which will maintain an adequate clinical response is reached. It should be kept in mind that constant monitoring is needed in regard to drug dosage. Included in the situations which may make dosage adjustments necessary are changes in clinical status secondary to remissions or exacerbations in the disease process, the patient's individual drug responsiveness, and the effect of patient exposure to stressful situations not directly related to the disease entity under treatment; in this latter situation it may be necessary to increase the dosage of MEDROL for a period of time consistent with the patient's condition. If after long-term therapy the drug is to be stopped, it is recommended that it be withdrawn gradually rather than abruptly.

Multiple Sclerosis:

In treatment of acute exacerbations of multiple sclerosis daily doses of 200 mg of prednisolone for a week followed by 80 mg every other day for 1 month have been shown to be effective (4 mg of methylprednisolone is equivalent to 5 mg of prednisolone).

ADT® (Alternate Day Therapy):

Alternate day therapy is a corticosteroid dosing regimen in which twice the usual daily dose of corticoid is administered every other morning. The purpose of this mode of therapy is to provide the patient requiring long-term pharmacologic dose treatment with the beneficial effects of corticoids while minimizing certain undesirable effects, including pituitary-adrenal suppression, the Cushingoid state, corticoid withdrawal symptoms, and growth suppression in children.

The rationale for this treatment schedule is based on two major premises: (a) the anti-inflammatory or therapeutic effect of corticoids persists longer than their physical presence and metabolic effects and (b) administration of the corticosteroid every other morning allows for reestablishment of more nearly normal hypothalamic-pituitary-adrenal (HPA) activity on the off-steroid day.

A brief review of the HPA physiology may be helpful in understanding this rationale. Acting primarily through the hypothalamus a fall in free cortisol stimulates the pituitary gland to produce increasing amounts of corticotropin (ACTH) while a rise in free cortisol inhibits ACTH secretion. Normally the HPA system is characterized by diurnal (circadian) rhythm. Serum levels of ACTH rise from a low point about 10 pm to a peak level about 6 am. Increasing levels of ACTH stimulate adrenal cortical activity resulting in a rise in plasma cortisol with maximal levels occurring between 2 am and 8 am. This rise in cortisol dampens ACTH production and in turn adrenal cortical activity. There is a gradual fall in plasma corticoids during the day with lowest levels occurring about midnight.

The diurnal rhythm of the HPA axis is lost in Cushing's disease, a syndrome of adrenal cortical hyperfunction characterized by obesity with centripetal fat distribution, thinning of the skin with easy bruisability, muscle wasting with weakness, hypertension, latent diabetes, osteoporosis, electrolyte imbalance, etc. The same clinical findings of hyperadrenocorticism may be noted during long-term pharmacologic dose corticoid therapy administered in conventional daily divided doses. It would appear, then, that a disturbance in the diurnal cycle with maintenance of elevated corticoid values during the night may play a significant role in the development of undesirable corticoid effects. Escape from these constantly elevated plasma levels for even short periods of time may be instrumental in protecting against undesirable pharmacologic effects.

During conventional pharmacologic dose corticosteroid therapy, ACTH production is inhibited with subsequent suppression of cortisol production by the adrenal cortex. Recovery time for normal HPA activity is variable depending upon the dose and duration of treatment. During this time the patient is vulnerable to any stressful situation. Although it has been shown that there is considerably less adrenal suppression following a single morning dose of prednisolone (10 mg) as opposed to a quarter of that dose administered every six hours, there is evidence that some suppressive effect on adrenal activity may be carried over into the following day when pharmacologic doses are used. Further, it has been shown that a single dose of certain corticosteroids will produce adrenal cortical suppression for two or more days. Other corticoids, including methylprednisolone, hydrocortisone, prednisone, and prednisolone, are considered to be short acting (producing adrenal cortical suppression for 1¼ to 1½ days following a single dose) and thus are recommended for alternate day therapy.

The following should be kept in mind when considering alternate day therapy:

1) Basic principles and indications for corticosteroid therapy should apply. The benefits of ADT should not encourage the indiscriminate use of steroids.
2) ADT is a therapeutic technique primarily designed for patients in whom long-term pharmacologic corticoid therapy is anticipated.
3) In less severe disease processes in which corticoid therapy is indicated, it may be possible to initiate treatment with ADT. More severe disease states usually will require daily divided high dose therapy for initial control of the disease process. The initial suppressive dose level should be continued until satisfactory clinical response is obtained, usually four to ten days in the case of many allergic and collagen diseases. It is important to keep the period of initial suppressive dose as brief as possible particularly when subsequent use of alternate day therapy is intended.
  Once control has been established, two courses are available: (a) change to ADT and then gradually reduce the amount of corticoid given every other day or (b) following control of the disease process reduce the daily dose of corticoid to the lowest effective level as rapidly as possible and then change over to an alternate day schedule. Theoretically, course (a) may be preferable.
4) Because of the advantages of ADT, it may be desirable to try patients on this form of therapy who have been on daily corticoids for long periods of time (eg, patients with rheumatoid arthritis). Since these patients may already have a suppressed HPA axis, establishing them on ADT may be difficult and not always successful. However, it is recommended that regular attempts be made to change them over. It may be helpful to triple or even quadruple the daily maintenance dose and administer this every other day rather than just doubling the daily dose if difficulty is encountered. Once the patient is again controlled, an attempt should be made to reduce this dose to a minimum.
5) As indicated above, certain corticosteroids, because of their prolonged suppressive effect on adrenal activity, are not recommended for alternate day therapy (eg, dexamethasone and betamethasone).
6) The maximal activity of the adrenal cortex is between 2 am and 8 am, and it is minimal between 4 pm and midnight. Exogenous corticosteroids suppress adrenocortical activity the least, when given at the time of maximal activity (am).
7) In using ADT it is important, as in all therapeutic situations to individualize and tailor the therapy to each patient. Complete control of symptoms will not be possible in all patients. An explanation of the benefits of ADT will help the patient to understand and tolerate the possible flare-up in symptoms which may occur in the latter part of the offsteroid day. Other symptomatic therapy may be added or increased at this time if needed.
8) In the event of an acute flare-up of the disease process, it may be necessary to return to a full suppressive daily divided corticoid dose for control. Once control is again established alternate day therapy may be reinstituted.
9) Although many of the undesirable features of corticosteroid therapy can be minimized by ADT, as in any therapeutic situation, the physician must carefully weigh the benefit-risk ratio for each patient in whom corticoid therapy is being considered.

HOW SUPPLIED

MEDROL Tablets are available in the following strengths and package sizes:

2 mg (white, elliptical, scored, imprinted MEDROL 2)

Bottles of 100 NDC 0009-0020-01

4 mg (white, elliptical, scored, imprinted MEDROL 4)

Bottles of 100 NDC 0009-0056-02

DOSEPAK™ Unit of Use (21 tablets) NDC 0009-0056-04

8 mg (white, elliptical, scored, imprinted MEDROL 8)

Bottles of 25 NDC 0009-0022-01

16 mg (white, elliptical, scored, imprinted MEDROL 16)

Bottles of 50 NDC 0009-0073-01

32 mg (white, elliptical, scored, imprinted MEDROL 32)

Bottles of 25 NDC 0009-0176-01

STORAGE AND HANDLING

Store at controlled room temperature 20° to 25°C (68° to 77°F) [see USP].

REFERENCES

^1 Fekety R. Infections associated with corticosteroids and immunosuppressive therapy. In: Gorbach SL, Bartlett JG, Blacklow NR, eds. Infectious Diseases. Philadelphia: WBSaunders Company 1992:1050–1.

^2 Stuck AE, Minder CE, Frey FJ. Risk of infectious complications in patients taking glucocorticoids. Rev Infect Dis 1989:11(6):954–63.

This product's label may have been updated. For current full prescribing information, please visit www.pfizer.com.

For medical information about MEDROL, please visit www.pfizermedinfo.com or call 1‑800‑438‑1985.

LAB-0157-13.0
Revised November 2025

PRINCIPAL DISPLAY PANEL - 4 mg Tablet Bottle Label

Pfizer

NDC 0009-0056-02

Medrol®
methylprednisolone
tablets, USP

4 mg

100 Tablets
Rx only

Distributed by
Pharmacia & Upjohn Company LLC
A Subsidiary of Pfizer Inc.
New York, NY 10007

PRINCIPAL DISPLAY PANEL - 4 mg Tablet Dose Pack

START HERE

DAY 1
Before Breakfast
Before Breakfast
After Lunch
After Dinner
At Bedtime
At Bedtime

DAY 2
Before Breakfast
After Lunch
After Dinner
At Bedtime
At Bedtime

DAY 3
Before Breakfast
After Lunch
After Dinner
At Bedtime

DAY 4
Before Breakfast
After Lunch
At Bedtime

DAY 5
Before Breakfast
At Bedtime

DAY 6
Before Breakfast

NDC 0009-0056-04

Medrol® Dosepak™
(methylprednisolone) tablets, USP
4 mg

Distributed by Pharmacia & Upjohn
Company LLC, A subsidiary of Pfizer Inc.,
New York, NY 10001

Unless otherwise directed by your physician, all six (6)
tablets in the row labeled DAY 1 should be taken the day
you receive your prescription, even though you may not
receive it until late in the day.

All six (6) tablets may be taken immediately as a single
dose, or may be divided into two or three doses and taken
at intervals between the time you receive the medicine and
your regular bedtime.

Rx only

Package Not Child-Resistant.
Keep Out of Reach of Children.

LOT: XXXXXXX
EXP: YYYY-MMM

PRINCIPAL DISPLAY PANEL - 4 mg Tablet Dose Pack Carton

NDC 0009-0056-04

Pfizer

Medrol® Dosepak™ 4 mg
(methylprednisolone) tablets, USP

Unit of Use

One blister containing 21 tablets

Rx only

PRINCIPAL DISPLAY PANEL - 8 mg Tablet Bottle Label

Pfizer

NDC 0009-0022-01

Medrol®
methylprednisolone
tablets, USP

8 mg

25 Tablets
Rx only

Distributed by
Pharmacia & Upjohn Company LLC
A Subsidiary of Pfizer Inc.
New York, NY 10001

PRINCIPAL DISPLAY PANEL - 16 mg Tablet Bottle Label

Pfizer

NDC 0009-0073-01

Medrol®
methylprednisolone
tablets, USP

16 mg

50 Tablets
Rx only

Distributed by
Pharmacia & Upjohn Company LLC
A Subsidiary of Pfizer Inc.
New York, NY 10001

PRINCIPAL DISPLAY PANEL - 32 mg Tablet Bottle Label

Pfizer

NDC 0009-0176-01

Medrol®
methylprednisolone
tablets, USP

32 mg

25 Tablets
Rx only

Distributed by
Pharmacia & Upjohn Co
Division of Pfizer Inc, NY, NY 10017

PRINCIPAL DISPLAY PANEL - 2 mg Tablet Bottle Label

Pfizer

NDC 0009-0020-01

Medrol®
methylprednisolone
tablets, USP

2 mg

100 Tablets
Rx only

Distributed by
Pharmacia & Upjohn Company LLC
A Subsidiary of Pfizer Inc.
New York, NY 10001